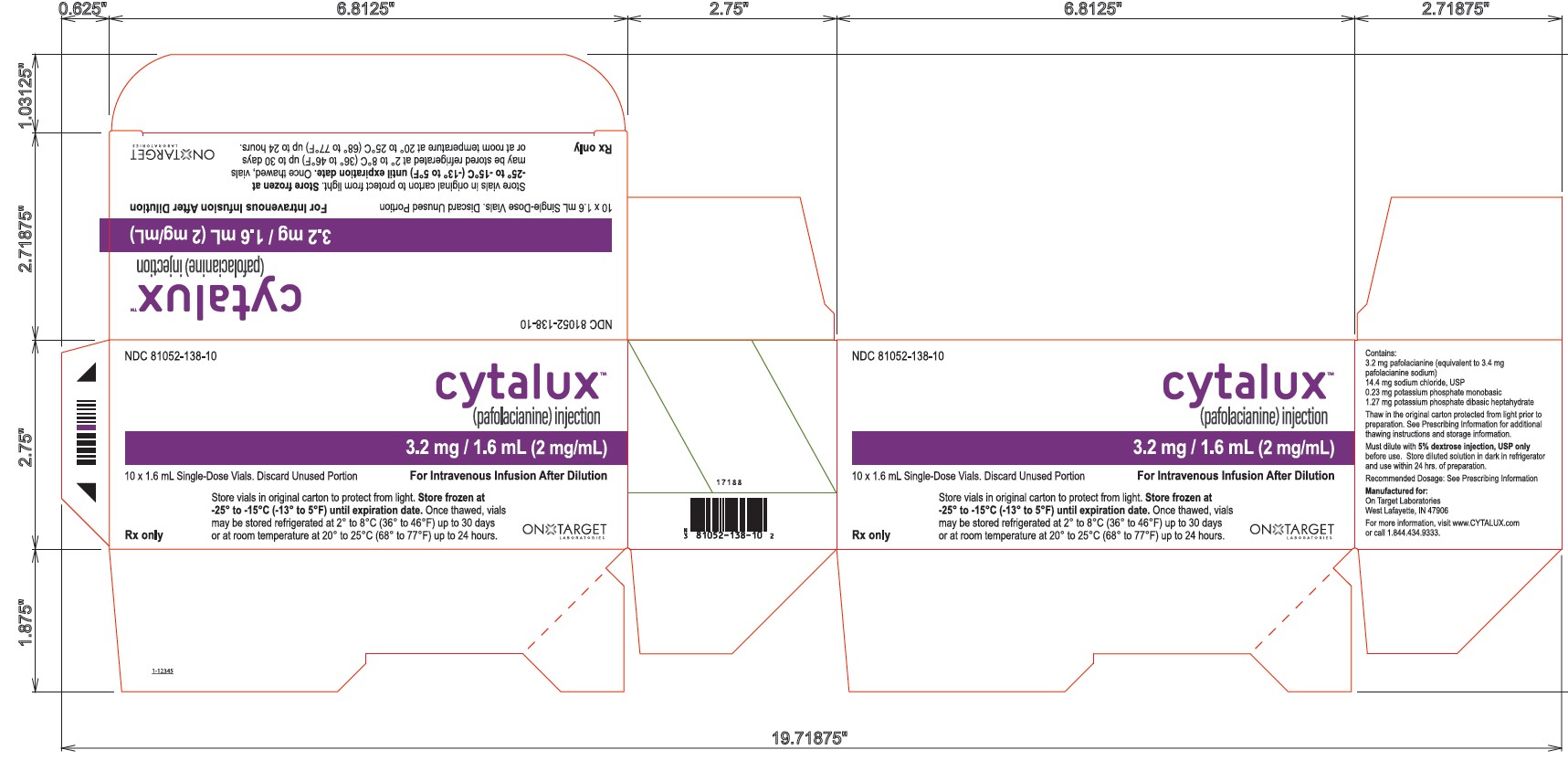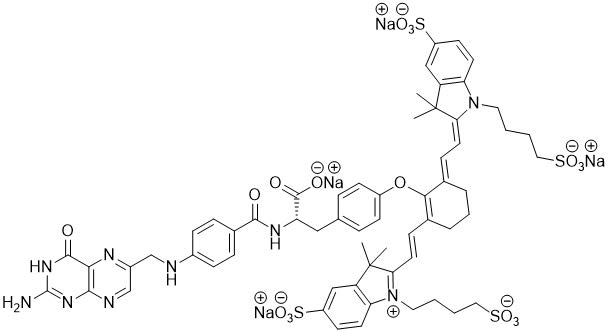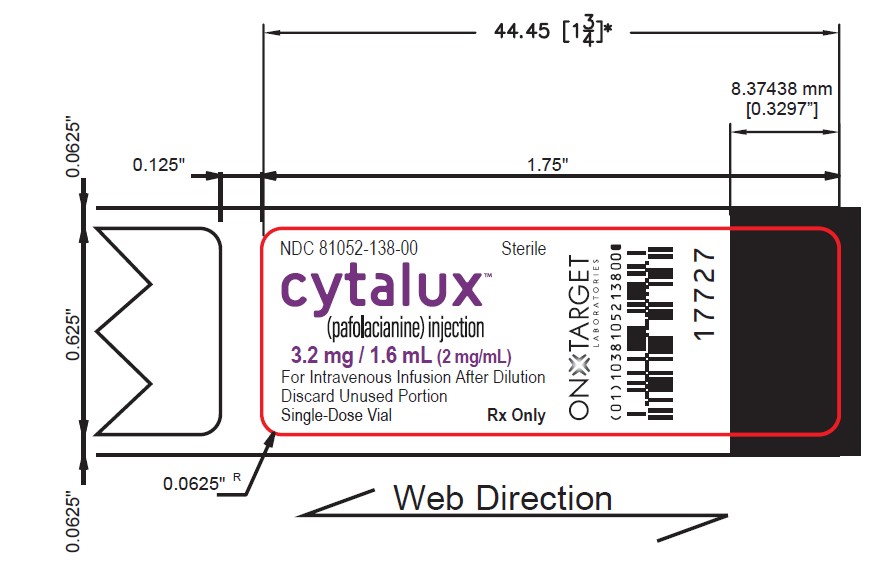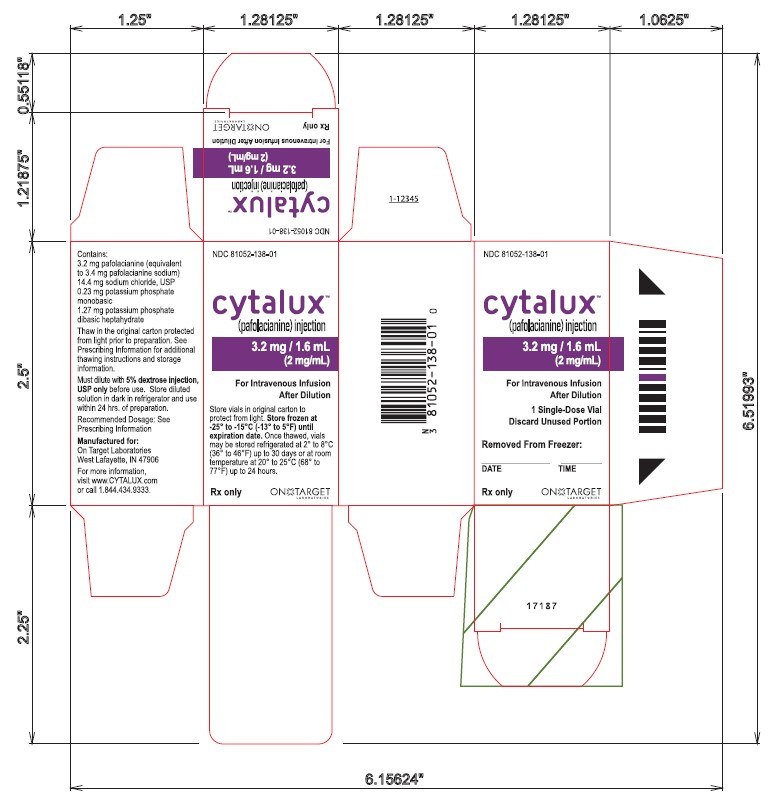 DRUG LABEL: Cytalux
NDC: 81052-138 | Form: INJECTION
Manufacturer: On Target Laboratories, Inc.
Category: prescription | Type: HUMAN PRESCRIPTION DRUG LABEL
Date: 20251022

ACTIVE INGREDIENTS: PAFOLACIANINE SODIUM 3.2 mg/1.6 mL
INACTIVE INGREDIENTS: WATER; SODIUM PHOSPHATE, DIBASIC, HEPTAHYDRATE; SODIUM CHLORIDE; HYDROCHLORIC ACID; POTASSIUM PHOSPHATE, MONOBASIC; SODIUM HYDROXIDE

HIGHLIGHTS OF PRESCRIBING INFORMATION

These highlights do not include all the information needed to use CYTALUX safely and effectively. See full prescribing information for CYTALUX.
CYTALUX® (pafolacianine) injection, for intravenous use
Initial U.S. Approval: 2021

RECENT MAJOR CHANGES

Dosage and Administration, 7/2025

Preparation and Storage Instructions (2.3)

1. INDICATIONS AND USAGE

CYTALUX is an optical imaging agent indicated as an adjunct for intraoperative identification of:

- Malignant lesions in adult patients with ovarian cancer.
- Malignant and non-malignant pulmonary lesions in adult patients with known or suspected cancer in the lung. (1)

2 DOSAGE AND ADMINISTRATION

- For recommended testing, evaluations, and premedications, see Full Prescribing Information. (2.1)

- Recommended intravenous dosage of CYTALUX is:
  - Adult Patients with Ovarian Cancer: 0.025 mg/kg over 60 minutes, 1 hour to 9 hours prior to surgery
  - Adult Patients with Known or Suspected Cancer in the Lung: 0.025 mg/kg over 60 minutes, 1 hour to 24 hours prior to surgery. (2.2)
- For preparation, management of infusion-related reactions, and imaging information see Full Prescribing Information. CYTALUX should only be used by trained surgeons using FDA cleared imaging systems. (2.3, 2.4, 2.5)

3 DOSAGE FORMS AND STRENGTHS

Injection: 3.2 mg/1.6 mL (2 mg/mL) of pafolacianine in a single-dose
vial. (3)

4 CONTRAINDICATIONS

None. (4)

5 WARNINGS AND PRECAUTIONS

- Infusion-Related Reactions: Interrupt the infusion and treat as

necessary with antihistamines and/or nausea medications. (5.1)

- Risk of misinterpretation: Non-fluorescing tissue in the surgical field

does not rule out the presence of tumor. Fluorescence may be seen
in non-cancerous tissues. (5.2)

- Embryo-Fetal Toxicity: CYTALUX may cause fetal harm. Advise

females of reproductive potential of the potential risk to a fetus. (5.3,
8.1, 8.3)

- Risk of Pafolacianine Aggregation and Infusion Reactions: Use only

5% Dextrose Injection for dilution. Do not use other diluents. (5.4)

6 ADVERSE REACTIONS

Most common adverse reactions (incidence ≥1%; ovarian and lung combined) included nausea, vomiting, abdominal pain, flushing, other infusion-related reactions, hypersensitivity, elevation in blood pressure, dyspepsia, and chest discomfort. (6)

To report SUSPECTED ADVERSE REACTIONS, contact On Target
Laboratories at 1-844-434-9333 or FDA at 1-800-FDA-1088 or
www.fda.gov/medwatch.

7 DRUG INTERACTIONS

Folate Supplements: Avoid folate, folic acid, or folate-containing
supplements within 48 hours before administration of CYTALUX. (7)

See 17 for PATIENT COUNSELING INFORMATION.

FULL PRESCRIBING INFORMATION

1. INDICATIONS AND USAGE

CYTALUX is indicated as an adjunct for intraoperative identification of:

- Malignant lesions in adult patients with ovarian cancer.
- Malignant and non-malignant pulmonary lesions in adult patients with known or suspected cancer in the lung.

2 DOSAGE AND ADMINISTRATION

2.1 Recommended Testing, Evaluations and Premedications Prior to Administration of CYTALUX

Obtain a pregnancy test in females of reproductive potential and verify the absence of pregnancy
prior to administration of CYTALUX [ see Warnings and Precautions (5.3) and Use in Specific
Populations (8.1, 8.3) ].
Discontinue folate, folic acid, or folate containing supplements 48 hours before administration of
CYTALUX [ see Drug Interactions (7)].
Consider administering antihistamines and/or anti-nausea medication for prophylaxis against infusion related
reactions [ see Warnings and Precautions (5.1)].

2.2 Recommended Dosage and Administration

Adult Patients with Ovarian Cancer

The recommended dose of CYTALUX is a single intravenous infusion of 0.025 mg/kg diluted in 250 mL of 5% Dextrose Injection, administered over 60 minutes using a dedicated infusion line, 1 hour to 9 hours prior to surgery.

Adult Patients with Known or Suspected Cancer in the Lung

The recommended dose of CYTALUX is a single intravenous infusion of 0.025 mg/kg diluted in 250 mL of 5% Dextrose Injection, administered over 60 minutes using a dedicated infusion line, 1 hour to 24 hours prior to surgery.

2.3 Preparation and Storage Instructions

Parenteral drug products should be inspected visually for particulate matter and discoloration prior to administration whenever solution and container permit.

1. Use aseptic technique for the preparation of CYTALUX infusion solution.

2. Only use 5% Dextrose Injection for dilution. Do not use other diluents due to incompatibility [see Warnings and Precautions (5.4)] .

3. CYTALUX vials should be stored and thawed in the original carton protected from light.

1. Remove carton containing one single vial of CYTALUX from freezer and record the date, time and thawing condition on the carton.
2. Thaw at room temperature between 20°C to 25°C (68°F to 77°F) for at least 60 minutes or under refrigerated conditions between 2°C to 8°C (36°F to 46°F) for at least 6 hours. When thawed under refrigerated conditions, allow the vial to stand at room temperature for 15 minutes before dilution.
3. Once thawed, an individual CYTALUX vial may be stored at room temperature between 20°C to 25°C (68°F to 77°F) for a maximum single period of 24 hours or under refrigerated conditions between 2°C to 8°C (36°F to 46°F) for a maximum single period of up to 30 days, prior to preparation for infusion.
4. If CYTALUX vial is not used within the maximum single period at either room temperature or under refrigerated conditions, the vial may be refrozen up to three times.
5. If the vial has been thawed after the third refreeze, it must be used. If not used after the third refreeze, do not use and discard the vial.
6. Each vial of CYTALUX may be penetrated only once at the time of preparation of infusion solution. Once penetrated, the vial may not be refrozen.

4. Hand shake or vortex the thawed CYTALUX vial for 60 seconds.

5. Withdraw the calculated volume of CYTALUX for a dose of 0.025 mg/kg. Discard any unused portion in the vial.

6. Add into a 250 mL of 5% Dextrose Injection, USP bag.

7. Gently swirl the bag by hand for 1 minute to mix the solution.

8. Visually inspect the infusion bag. The solution should be light blue/green to clear in color and should not contain any visible particulate matter.

9. Protect the infusion bag from light using a light-blocking cover during infusion and storage.

10. If not immediately used, store the diluted CYTALUX infusion solution in a refrigerator at 2°C to 8°C (36°F to 46°F) for not more than 24 hours. Once the bag is removed from refrigeration, infusion must be completed within 3 hours.

2.4 Management of Infusion-Related Reactions

If the patient develops an infusion reaction during administration, interrupt the infusion and treat with
antihistamines and/or anti-nausea medication as necessary, based on clinical decision. Complete the
infusion within 3 hours of the start of the initial administration [ see Warnings and Precautions (5.1)].

2.5 Imaging

- Clinical data demonstrate that near infrared (NIR) imaging devices that excite at 760 nm to 785 nm and detect emission at 790 nm to 815 nm are suitable for use with CYTALUX.
- CYTALUX is to be used with an NIR imaging system cleared by the FDA for specific use with pafolacianine.
- CYTALUX should only be used by surgeons who have completed a training program on the use of NIR imaging systems for fluorescence imaging during surgery. Training is provided by the device manufacturer.

3 DOSAGE FORMS AND STRENGTHS

Injection: 3.2 mg/1.6 mL (2 mg/mL) pafolacianine (equivalent to 3.4 mg/1.6 mL pafolacianine sodium)
supplied as a dark bluish green, clear aqueous solution in a single-dose vial.

4 CONTRAINDICATIONS

None.

5 WARNINGS AND PRECAUTIONS

5.1 Infusion-Related Reactions

Adverse reactions including nausea, vomiting, abdominal pain, flushing, hypersensitivity, elevation in blood pressure, dyspepsia, and chest discomfort were reported in patients receiving CYTALUX in clinical studies. A total of 17% of patients experienced reactions during the administration of CYTALUX [see Adverse Reactions (6.1)] . Reactions typically occurred within 15 minutes of the start of infusion. CYTALUX infusion interruption or discontinuation due to adverse reactions occurred in 11% of all patients. Treatment with antihistamines and/or anti-nausea medication may be used. If an adverse reaction occurs during administration, the infusion can be interrupted and resumed after treatment of the reaction [see Dosage and Administration (2.1, 2.4)] .

5.2 Risk of Misinterpretation

Errors may occur with the use of CYTALUX during intraoperative fluorescence imaging to detect ovarian cancer and lesions in the lung, including false negatives and false positives. Non-fluorescing tissue in the surgical field does not rule out the presence of ovarian cancer or lesions in the lung [see Clinical Studies (14)]. Fluorescence may be seen in normal tissues including bowel, kidneys, lymph nodes, and lungs as well as in inflamed tissues.

5.3 Embryo-Fetal Toxicity

Based on its mechanism of action, CYTALUX may cause fetal harm when administered to a pregnant
woman. Advise females of reproductive potential of the potential risk to a fetus. Verify pregnancy
status of females of reproductive potential prior to initiating CYTALUX treatment. [ see Use in Specific
Populations (8.1, 8.3), Clinical Pharmacology (12.1) ].

5.4 Risk of Pafolacianine Aggregation and Infusion Reactions

Use of the incorrect diluent to prepare the CYTALUX infusion solution can cause the aggregation of
pafolacianine; aggregation may induce infusion reactions, such as nausea, vomiting, abdominal pain
or rash. Use only 5% Dextrose Injection to prepare the CYTALUX infusion solution. Do not use other
diluents. [see Dosage and Administration (2.3)].

6 ADVERSE REACTIONS

The following clinically significant adverse reaction is described elsewhere in the labeling:
• Infusion-Related Reactions [ see Warnings and Precautions (5.1) ]

6.1 Clinical Trials Experience

Because clinical trials are conducted under widely varying conditions, adverse reaction rates observed in the clinical trials of a drug cannot be directly compared to rates in the clinical trials of another drug and may not reflect the rates observed in practice.

The safety of CYTALUX was evaluated in four open label clinical studies, two studies (N = 44 and N = 150) in patients with ovarian cancer and two studies (N = 100 and N = 112) in patients with known or suspected cancer in the lung. A total of 406 patients received 0.025 mg/kg of CYTALUX via intravenous administration.

The demographic characteristics of the study population were 82% female (66% female in lung studies), mean age 64 years (range 26 to 89 years), 85% White, 6% Black or African American, 5% Asian, and 4% other race, 5% Hispanic or Latino, 92% Not Hispanic or Latino, and 3% unreported ethnicity.

Adverse reactions that occurred in > 1% of patients are presented in Table 1.

Table 1. Adverse Reactions from Clinical Studies Reported in ≥ 1% of CYTALUX Treated Patients with Ovarian Cancer or Known or Suspected Cancer in the Lung

Adverse Reaction | CYTALUX 0.025 mg/kg; (N = 406); %
Nausea | 13
Vomiting | 5
Abdominal pain | 2
Flushing | 2
Other infusion-related reactions | 2
Hypersensitivity | 2
Elevation in blood pressure | 1
Dyspepsia | 1
Chest discomfort | 1

Adverse reactions occurred during the administration of CYTALUX in 17% of patients.

Overall, the safety profile observed in patients treated with CYTALUX 0.025 mg/kg was similar between patients with ovarian cancer and patients with known or suspected cancer in the lung.

7 DRUG INTERACTIONS

Use of folate, folic acid, or folate-containing supplements may reduce binding of pafolacianine to
folate receptors and could reduce the detection of lesions with CYTALUX. Avoid administration of
folate, folic acid, or folate-containing supplements within 48 hours before administration of CYTALUX [see Dosage and Administration (2.1) and Clinical Pharmacology (12.1)].

8 USE IN SPECIFIC POPULATIONS

8.1 Pregnancy

Risk Summary
Based on its mechanism of action, pafolacianine may cause fetal harm when administered to a
pregnant woman [see Clinical Pharmacology (12.1)]. There are no available human data to evaluate
for a drug-associated risk of major birth defects, miscarriage, or other adverse maternal or fetal outcomes.
No adverse developmental effects were observed in rats and rabbits with intravenous administration
of pafolacianine during organogenesis (embryofetal development) at doses up to 158-fold (rat) and 570-fold (rabbit) the recommended human dose of 0.025 mg/kg based on AUC, otherwise 9.6 and
38.4-fold based on human equivalent dose (HED) (see Data).
The estimated background risk of major birth defects and miscarriage for the indicated populations
are unknown. All pregnancies have a background risk of birth defects, loss, or other adverse
outcomes. In the U.S. general population, the estimated background risk of major birth defects and
miscarriage in clinically recognized pregnancies is 2% to 4% and 15% to 20%, respectively.

Data
Animal Data
In the definitive embryo-fetal development (EFD) studies, pafolacianine was intravenously
administered during the period of organogenesis as follows: 0.015, 0.15, and 1.5 mg/kg/day from
gestational day (GD) 6 to GD17 in rats (HEDs of 0.002, 0.024 and 0.242 mg/kg/day), and 0.3, 1, and
3 mg/kg/day from GD7 to GD20 in rabbits (HEDs of 0.097, 0.323 and 0.968 mg/kg/day). No
significant drug-related maternal toxicity and embryo-fetal development toxicity were observed.
NOAELs were 1.5 mg/kg/day in rats and 3 mg/kg/day in rabbits. Estimated systemic exposures were
158 times (rat) and 570 times (rabbit) the human exposure at a human dose of 0.025 mg/kg based on
plasma AUC comparison.

8.2 Lactation

Risk Summary
There are no data on the presence of pafolacianine in either human or animal milk, the effects on the
breastfed infant, or the effects on milk production. The developmental and health benefits of
breastfeeding should be considered along with the mother’s clinical need for CYTALUX and any
potential adverse effects on the breastfed infant from CYTALUX or from the underlying maternal
condition.

8.3 Females and Males of Reproductive Potential

CYTALUX may cause fetal harm if administered to a pregnant woman [see Warnings And
Precautions (5.3) and Use in Specific Populations (8.1)].

Pregnancy Testing
Obtain a pregnancy test in females of reproductive potential and verify the absence of
pregnancy prior to administration of CYTALUX [see Dosage and Administration (2.1)].

8.4 Pediatric Use

Safety and effectiveness of CYTALUX in pediatric patients have not been established.

8.5 Geriatric Use

Of the total number of patients in clinical studies of CYTALUX, 221 patients (54%) were 65 years of
age and older: 153 (38%) were 65 to 74 years of age, 66 (16%) were 75 to 84 years of age, and 2
(0.5%) were 85 years of age and older. No overall differences in safety, effectiveness, or
pharmacokinetics were observed between patients 65 years of age and older and younger adult
patients.

11 DESCRIPTION

CYTALUX contains pafolacianine, an optical imaging agent, as a tetrasodium salt referred to as
pafolacianine sodium. Chemically, pafolacianine sodium is (S)-2-(4-(((2-amino-4-oxo-3,4-
dihydropteridin-6-yl)methyl)amino)benzamido)-3-(4-(((E)-2-((E)-2-(3,3-dimethyl-5-sulfonato-1-(4-
sulfonatobutyl)-3H-indol-1-ium-2-yl)vinyl)-6-((E)-2-(3,3-dimethyl-5-sulfonato-1-(4-
sulfonatobutyl)indolin-2-ylidene)ethylidene)cyclohex-1-en-1-yl)oxy)phenyl)propanoate hydrate
tetrasodium. Pafolacianine sodium has a molecular formula of C61H63N9Na4O17S4, a molecular mass
of 1414.42 g/mol and has the following structure:

CYTALUX (pafolacianine) injection is a sterile, non-pyrogenic, dark bluish green, clear aqueous
solution for intravenous use. Each vial contains 3.2 mg (2 mg/mL) pafolacianine (equivalent to 3.4 mg
pafolacianine sodium),14.4 mg sodium chloride, 0.23 mg potassium phosphate monobasic, 1.27 mg
sodium phosphate dibasic heptahydrate in 1.6 mL volume. The pH is adjusted with sodium hydroxide
and/or hydrochloric acid and is between 7.1 to 7.8.

12 CLINICAL PHARMACOLOGY

12.1 Mechanism of Action

Pafolacianine binds to alpha and beta folate receptors (FR) on cells, is internalized via receptor-mediated endocytosis, and accumulates intracellularly.

Pafolacianine enhances lesion visualization through the differential level of expression and accessibility of folate receptors within lesions relative to normal tissue.

Pafolacianine absorbs light in the near-infrared (NIR) region within a range of 760 nm to 785 nm with peak absorption of 776 nm and emits fluorescence within a range of 790 nm to 815 nm with peak emission of 796 nm.

12.2 Pharmacodynamics

Tumor to background ratios of fluorescence intensity changed with different mass doses studied in patients with ovarian cancer. High tumor to background ratio was observed with 0.025 mg/kg dose. CYTALUX exposure-response relationships and the time course of pharmacodynamic responses are unknown.

12.3 Pharmacokinetics

The mean Cmax of pafolacianine was 59.1 ± 5.94 ng/mL and AUCinf was 63.6 ± 12.6 ng.hr/mL.
Distribution
The mean volume of distribution (Vz) is 17.1 ± 5.99 L, indicating distribution into tissues.
Plasma protein binding of pafolacianine is 93.7%. No notable partitioning into red blood cells has
been observed.
Elimination
The elimination half-life of pafolacianine is 0.44 ± 0.23 hours and mean plasma clearance is 28.6 ±
4.97 L/hr.
Metabolism
Pafolacianine sodium is not metabolized by cytochrome P450 (CYP) enzymes.
Excretion
Following a single IV infusion of radiolabeled pafolacianine sodium, approximately 35% of the dose
was recovered in urine (19.1%) and in feces (15.8%) after approximately 3-5 weeks.
Specific Populations
No clinically significant differences in pharmacokinetics of pafolacianine were identified based on age
18 to 89 years, weight 41.6 to 133.6 kg, mild to moderate renal impairment (CLcr 30 to 89 mL/min),
mild to moderate hepatic impairment (total bilirubin < 3 ULN and AST > ULN). The effect of severe
renal impairment (CLcr < 30 mL/min) and severe hepatic impairment (total bilirubin > 3 ULN and any
AST value) on the pharmacokinetics of pafolacianine have not been studied.
Drug Interaction Studies
No clinical studies evaluating the drug interaction potential of pafolacianine have been conducted.
In Vitro Studies
CYP Enzymes: Pafolacianine is not an inhibitor of CYPs 1A2, 2B6, 2C8, 2C9, 2C19 2D6, 3A4/5.
UDP-glucuronosyltransferase (UGT) Enzymes: Pafolacianine is not an inhibitor of UGT1A1.
Transporter Systems: Pafolacianine is a substrate for OATP1B1, OATP1B3, and OAT1. Pafolacianine
is not an inhibitor of OATP1B1, OATP1B3, OAT1, OAT3, OCT2, MATE1, MATE2-K, P-gp, or BCRP

13 NONCLINICAL TOXICOLOGY

13.1 Carcinogenesis, Mutagenesis, Impairment of Fertility

Carcinogenesis
No carcinogenicity studies of pafolacianine have been conducted.
Mutagenesis
No genotoxic hazards were identified when pafolacianine was evaluated in a standard testing battery
consisting of a bacterial reverse mutation assay, an in vitro micronucleus study conducted in Chinese
Hamster Ovary (CHO) cells, and a rat bone marrow micronucleus study.
Impairment of Fertility
Reproductive and developmental toxicity (fertility and embryonic development, pre- and postnatal
development) studies in animals have not been performed to evaluate the effects of pafolacianine on
fertility.

14 CLINICAL STUDIES

14.1 Patients with Known or Suspected Ovarian Cancer

The safety and efficacy of CYTALUX were evaluated in a randomized, multicenter, open-label study (NCT03180307). The study enrolled 178 women with a diagnosis or high clinical suspicion of ovarian cancer scheduled to undergo primary surgical cytoreduction, interval debulking, or recurrent ovarian cancer surgery. One hundred and fifty women received CYTALUX (dosed at 0.025 mg/kg at least 1 hour before initiation of fluorescence imaging). Among them, 134 women underwent both normal light and CYTALUX evaluation (Intent-to-Image Set). The demographic characteristics were mean age 60 (range 33 to 81) years, 85% White, 4% Asian, 5% Black or African American, 3% American Indian or Alaska native, 3% other races, 11% Hispanic or Latino, and 2% unreported ethnicity.

Table 2 shows the proportion of patients with at least one evaluable ovarian cancer lesion confirmed by central histopathology that was detected with CYTALUX but not with normal light or palpation and not otherwise identified for resection prior to surgery. The detection performance met the pre-specified success threshold.

Table 2: Detection Proportion with CYTALUX but Not with Normal Light or Palpation in the Intent-To-Image Set

N=134 patients | Patients with at least one confirmed ovarian cancer evaluable lesion
Number (n) | 36
Proportion (%); 95% CI | 0.269 (26.9%); (0.196*, 0.352)

*The pre-specified lower bound of the 95% confidence interval (CI) was 0.10.

In 20.2% (95% CI: 13.7%, 28.0%) of patients, all lesions detected by CYTALUX alone were negative by central histopathology (false positive).

14.2 Patients with Known or Suspected Cancer in the Lung

The safety and efficacy of CYTALUX were evaluated in a randomized, multicenter, open-label study (NCT04241315). The study enrolled 140 patients scheduled to undergo thoracoscopic or open segmental or subsegmental resection for primary lung lesions that were either confirmed or suspected to be cancer. One hundred and twelve patients received CYTALUX (dosed at 0.025 mg/kg between 1 and 24 hours before initiation of fluorescence imaging). Among them, 100 patients underwent both normal light and CYTALUX evaluation (Intent-to-Image Set). The demographic characteristics were 61% female, mean age 66 (range 26 to 83) years, 88% White, 8% Black or African American, 2% Asian, 2% other races, 99% Not Hispanic or Latino, and 1% unreported ethnicity. Histopathology of the primary lung lesions in these 100 patients showed primary lung cancer in 65%, metastasis to the lung in 21%, benign lung lesions in 11%, and other/unknown cancer in 3%. Among the primary lung cancers, 86% were adenocarcinoma, 8% were squamous cell carcinoma, 3% were adeno-squamous carcinoma, and 3% were atypical carcinoid.

Table 3 shows the proportion of patients in whom at least one of the following clinically significant events (CSE) occurred with CYTALUX but not with normal light or palpation: localization of the primary lung lesion, whether benign or malignant (CSE A), and detection of one or more synchronous malignant lung lesions (CSE B). Synchronous lesions were not identified prior to surgery. The combined CSE A and CSE B detection performance met the pre-specified success threshold.

Table 3: Proportion of Clinically Significant Events Occurring with CYTALUX but Not with Normal Light or Palpation in the Intent-To-Image Set

N=100 patients | Primary Lung Lesion (CSE A) | Synchronous Malignant Lung Lesion (CSE B) | Patients with CSE A and/or CSE B
Number (n) | 19* | 8 | 24**
Proportion (%); 95% CI | 0.19 (19%); (0.118, 0.281) | 0.08 (8%); (0.035, 0.152) | 0.24 (24%); (0.160***, 0.336)

* Including two subjects with benign primary lesions.

** Three patients had both primary lesion localization and synchronous malignant lesion detection, resulting in 27 events in 24 unique patients.

*** The pre-specified lower bound of the 95% confidence interval (CI) was 0.10.

CYTALUX did not identify the primary lung lesion in 23% (95% CI:15%, 32%) of patients. Among the 20 patients who had synchronous lesions detected only by CYTALUX, 12 patients had only benign synchronous lesions.

The depth of primary lung lesions detected by CYTALUX ranged from 0 to 38 mm from the lung surface (mean depth 6 mm).

16 HOW SUPPLIED/STORAGE AND HANDLING

How Supplied
CYTALUX (pafolacianine) injection, 3.2 mg /1.6 mL (2 mg/mL), is a dark bluish green, clear aqueous
solution packaged in a sealed amber glass single-dose vial. It is supplied in a carton containing 10
vials (NDC 81052-138-10) individually packaged.

Storage and Handling
Store vials in their original cartons to protect from light.

CYTALUX may be stored according to the table below. If CYTALUX vial is not used within the maximum single period at either room temperature or under refrigerated conditions the vial may be refrozen up to three time.

Storage Condition | Condition Temperature Range | Maximum Single Period | Permissible Freeze-Thaw Cycles
Frozen | -25°C to -15°C (-13°F to 5°F) | Until Expiration Date | Not applicable
Refrigeration | 2°C to 8°C (36°F to 46°F) | Up to 30 days | Three
Room Temperature | 20°C to 25°C (68°F to 77°F) | Up to 24 hours | Three

Do not use the product past the expiration date

17 PATIENT COUNSELING INFORMATION

Embryo-Fetal Toxicity
Advise females of reproductive potential of the potential risk to a fetus and to contact their healthcare
provider with a known or suspected pregnancy
[ see Warnings and Precautions (5.3) and Use In Specific Populations (8.1) ].

Folate Supplements Usage
Inform patients that folic acid may reduce the detection of cancer tissue with CYTALUX. Advise the
patient to stop taking folate, folic acid, or folate-containing supplements 48 hours before
administration of CYTALUX [ see Dosage and Administration (2.1) and Drug Interactions (7) ].

Manufactured by:

Grand River Aseptic Manufacturing

140 Front Ave SW

Grand Rapids, MI 49504

Manufactured for:

On Target Laboratories

1281 Win Hentschel Blvd

West Lafayette, IN 47906

PACKAGING - PRINCIPAL DISPLAY PANEL

10 Vial Carton

NDC 81052-138-10

cytalux™
(pafolacianine) injection

3.2 mg / 1.6 mL (2 mg/mL)

10 x 1.6 mL Single-Dose Vials. Discard Unused Portion
For Intravenous Infusion After Dilution

Store vials in original carton to protect from light. Store frozen at
-25° to -15°C (-13° to 5°F) until expiration date. Once thawed, vials

may be stored refrigerated at 2° to 8°C (36° to 46°F) up to 30 days

or at room temperature at 20° to 25°C (68° to 77°F) up to 24 hours.

Rx only

ON TARGET LABORATORIES

Vial Label

NDC 81052-138-10

Sterile

cytalux™
(pafolacianine) injection

3.2 mg / 1.6 mL
(2 mg/mL)

For Intravenous Infusion After Dilution

Discard Unused Portion

Single-Dose Vial

Rx only

ON TARGET LABORATORIES

17727

LOT:
EXP: YYYY/MM

Single Vial Carton Label

NDC 81052-138-01

cytalux™
(pafolacianine) injection

3.2 mg / 1.6 mL
(2 mg/mL)

For Intravenous Infusion After Dilution

Store vials in original carton to
protect from light. Store frozen at
-25° to -15°C (-13° to 5°F) until
expiration date. Once thawed, vials
may be stored refrigerated at 2° to 8°C
(36° to 46°F) up to 30 days or at room
temperature at 20° to 25°C (68° to
77°F) up to 24 hours.

Rx only

ON TARGET LABORATORIES